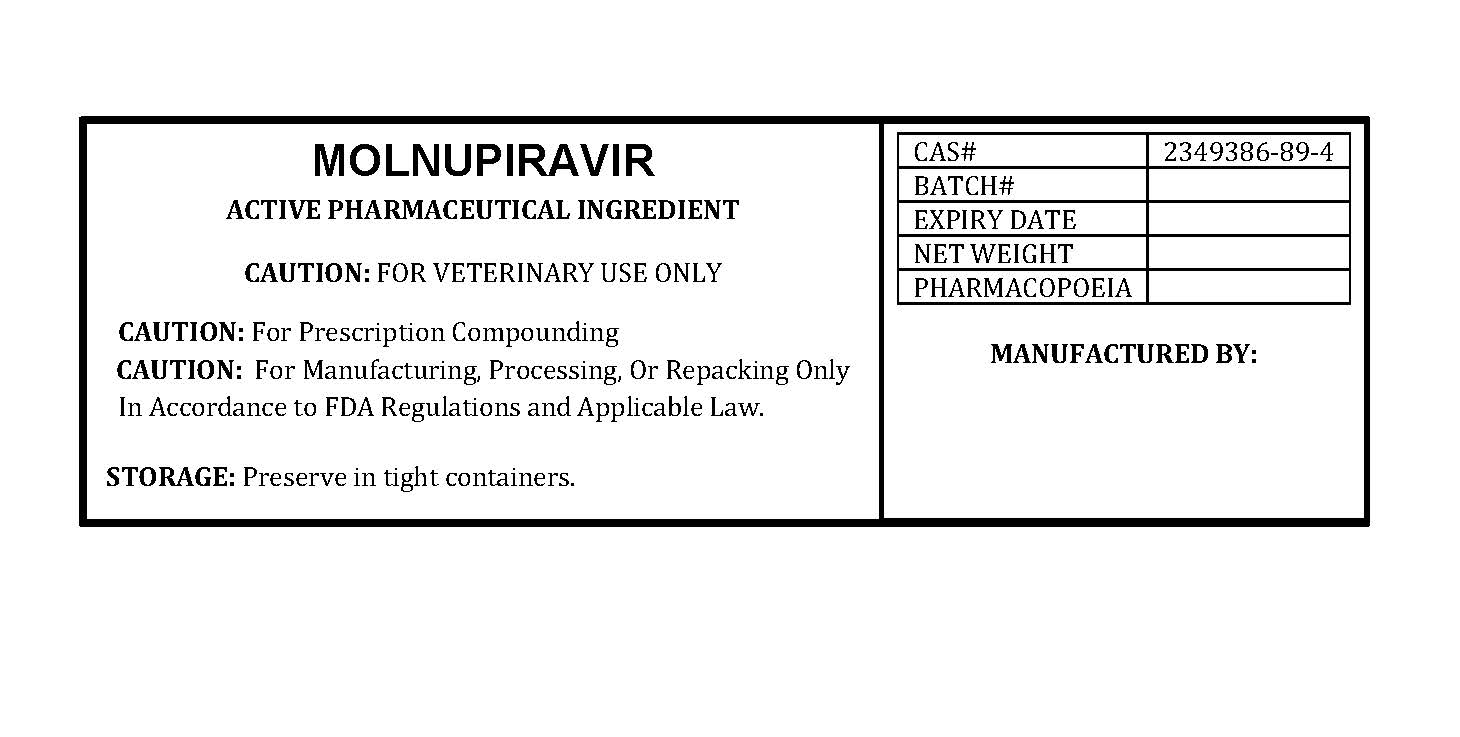 DRUG LABEL: MOLNUPIRAVIR
NDC: 86184-251 | Form: POWDER
Manufacturer: MAEDA INC
Category: other | Type: BULK INGREDIENT - ANIMAL DRUG
Date: 20260218

ACTIVE INGREDIENTS: MOLNUPIRAVIR 1 g/1 g

MOLNUPIRAVIR

PACKAGE LABEL

molnupiravirlabelfile.jpg